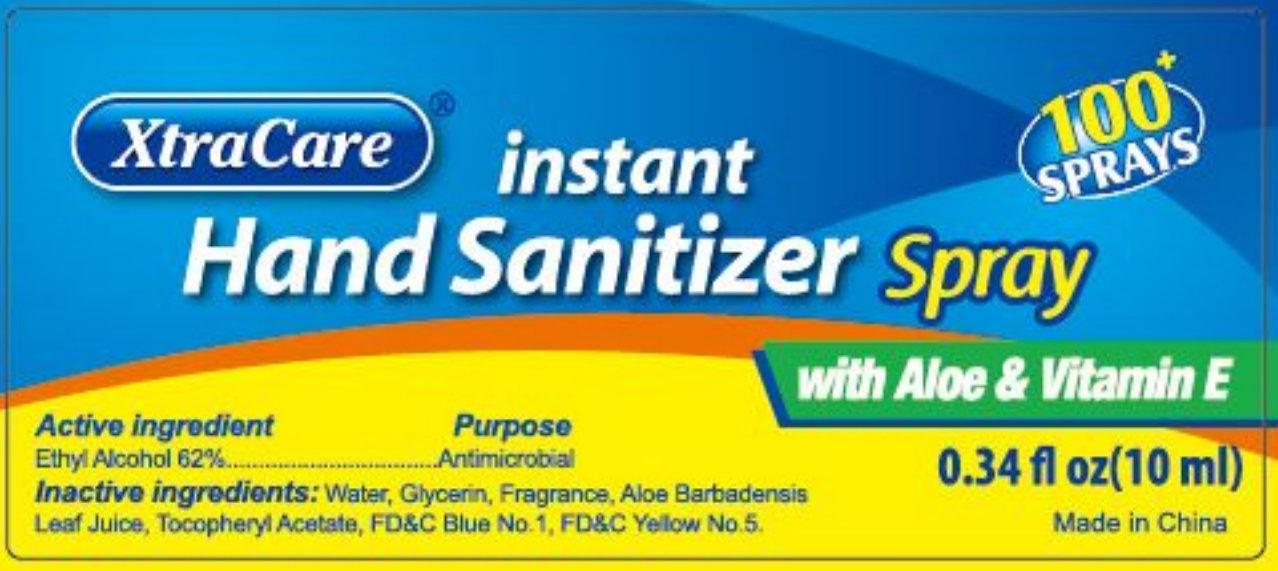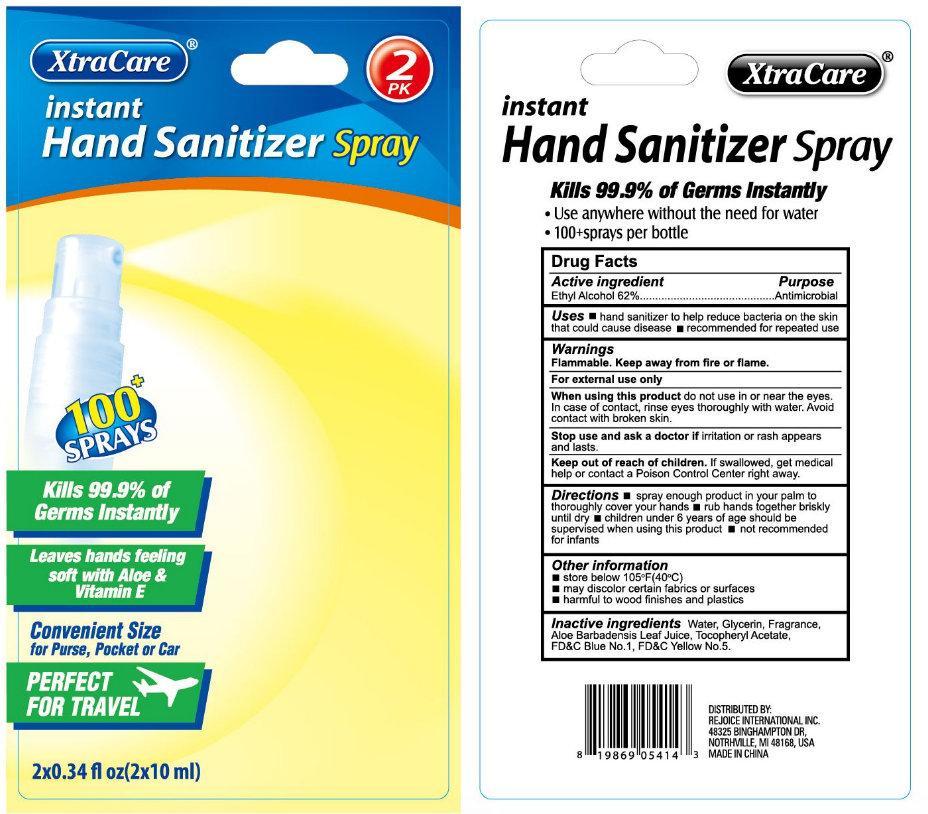 DRUG LABEL: XtraCare instant Hand Sanitizer
NDC: 57337-001 | Form: SPRAY
Manufacturer: Rejoice International
Category: otc | Type: HUMAN OTC DRUG LABEL
Date: 20130228

ACTIVE INGREDIENTS: ALCOHOL 62 mL/100 mL
INACTIVE INGREDIENTS: WATER; GLYCERIN; ALOE VERA LEAF; .ALPHA.-TOCOPHEROL ACETATE; FD&C BLUE NO. 1; FD&C YELLOW NO. 5

XtraCare instant Hand Sanitizer Spray

Active ingredient

Ethyl Alcohol 62%

Purpose

Antimicrobial

Uses

- hand sanitizer to help reduce bacteria on the skin that may cause disease.
- recommended for repeated use

Warnings

Flammable. Keep away from fire or flame.
For external use only

When using this product

do not use in or near the eyes. In case of contact, rinse eyes thoroughly with water. Avoid contact with broken skin.

Stop use and ask a doctor if

irritation or rash appears and lasts.

Keep out of reach of children.

if swallowed, get medical help or contact a Poison Control Center right away.

Directions

- spray enough product in your palm to thoroughly cover your hands
- rub hands together briskly until dry
- children under 6 years of age should be supervised when using this product
- not recommended for infants

Other Information

- store below 105^0F (40^0C)
- may discolor certain fabrics or surfaces
- harmful to wood finishes and plastics

Inactive ingredients

Water, Glycerin, Fragrance, Aloe Barbadensis Leaf Juice, Tocopheryl Acetate, FDandC Blue No. 1, FDandC Yellow No. 5.

XtraCare

instant Hand Sanitizer Spray Kills 99.9% of Germs Instantly

- Use anywhere without the need for water
- 100+sprays per bottle

DISTRIBUTED BY: REJOICE INTERNATIONAL INC. 48325 BINGHAMPTON DR, NOTRHVILLE, MI 48168, USA
MADE IN CHINA.

PACKAGE LABEL

XtraCare instant Hand Sanitizer Spray 2 PK 100+SPRAYS Kills 99.9% of Germs Instantly Leaves hands feeling soft with Aloe and Vitamin E Convenient Size for Purse, Pocket or Car PERFECT FOR TRAVEL 2x0.34 fl oz(2x10 ml)